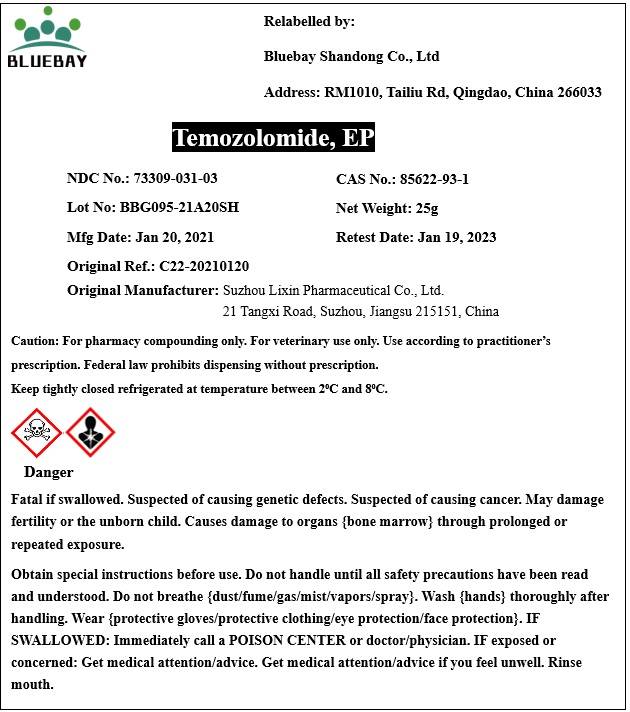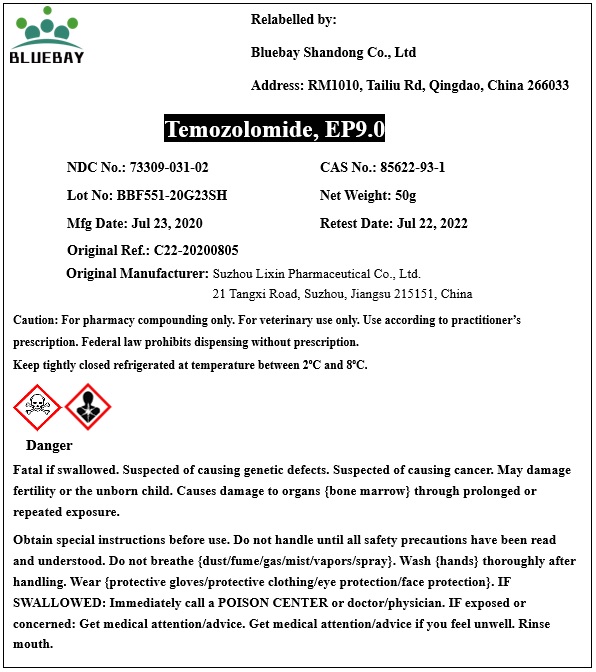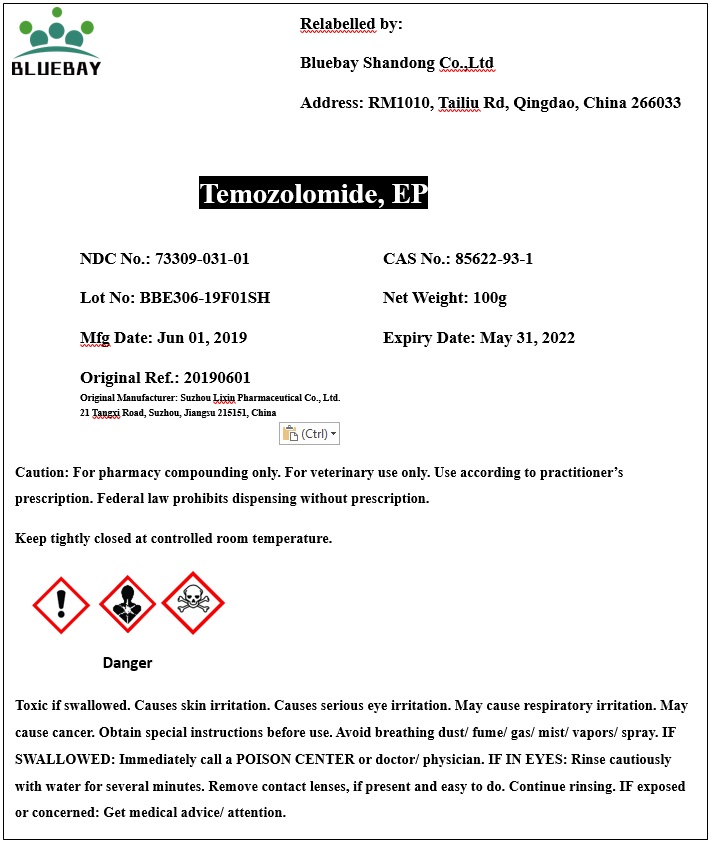 DRUG LABEL: Temozolomide
NDC: 73309-031 | Form: POWDER
Manufacturer: BLUEBAY SHANDONG CO.,LTD
Category: other | Type: BULK INGREDIENT
Date: 20210224

ACTIVE INGREDIENTS: TEMOZOLOMIDE 1 g/1 g

Temozolomide